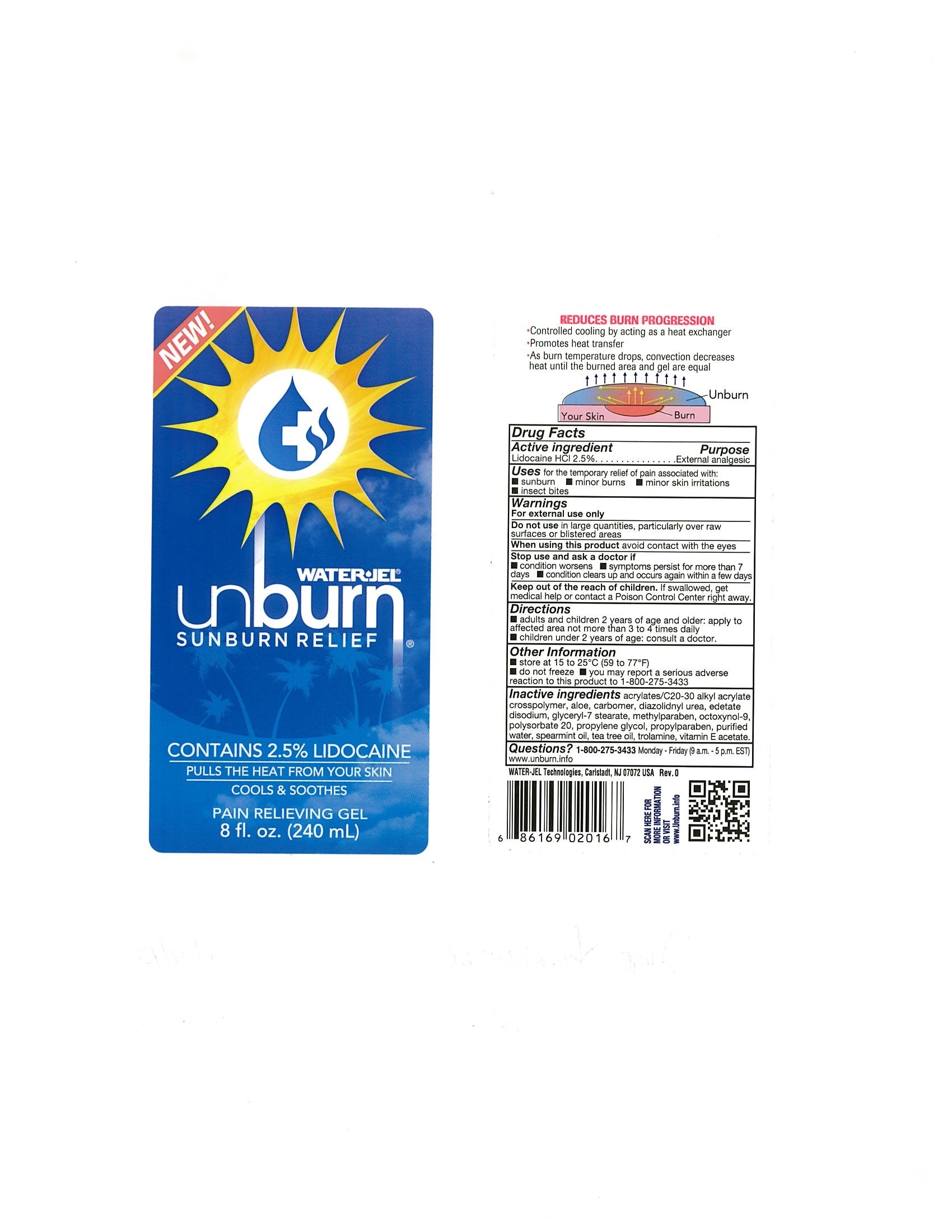 DRUG LABEL: Unburn
NDC: 59898-500 | Form: GEL
Manufacturer: Water-Jel Technologies
Category: otc | Type: HUMAN OTC DRUG LABEL
Date: 20171201

ACTIVE INGREDIENTS: LIDOCAINE HYDROCHLORIDE 2.5 g/100 mL
INACTIVE INGREDIENTS: METHYLPARABEN; OCTOXYNOL-9; POLYSORBATE 20; PROPYLENE GLYCOL; PROPYLPARABEN; WATER; SPEARMINT OIL; TEA TREE OIL; TROLAMINE; .ALPHA.-TOCOPHEROL ACETATE; CARBOMER HOMOPOLYMER TYPE C (ALLYL PENTAERYTHRITOL CROSSLINKED)

Water-Jel Unburn

Active ingredient

Lidocaine HCl 2.5%

Purpose

External analgesic

Uses

for the temporary relief of pain associated with:

- sunburn
- minor burns
- minor skin irritations
- insect bites

Warnings

For external use only

Do not use

- in large quantities, particularly over raw surfaces or blistered areas

When using this product

- avoid contact with eyes

Stop use and ask a doctor if

- condition worsens
- symptoms persist for more than 7 days
- condition clears up and occurs again within a few days

Keep out of the reach of children

If swallowed, get medical help or contact a Poison Control Center right away.

Directions

- adults and children 2 years of age and older; apply to affected area not more than 3 to 4 times daily
- children under 2 years of age: consult a doctor

Other information

- store at 15o to 25oC (59o to 77oF)
- do not freeze
- you may report a serious adverse reaction to this product to 1-800-275-3433

Inactive ingredients

acrylates/C20-30 alkyl acrylate crosspolymer, aloe, carbomer, diazolidnyl urea, edetate disodium, glyceryl-7 stearate, methylparaben, octoxynol-9, polysorbate 20, propylene glycol, propylparaben, purified water, spearmint oil, tea tree oil, trolamine, vitamin E acetate

QUESTIONS

1-800-275-3433

Monday - Friday (9a.m. - 5 p.m. EST)

www.unburn.info